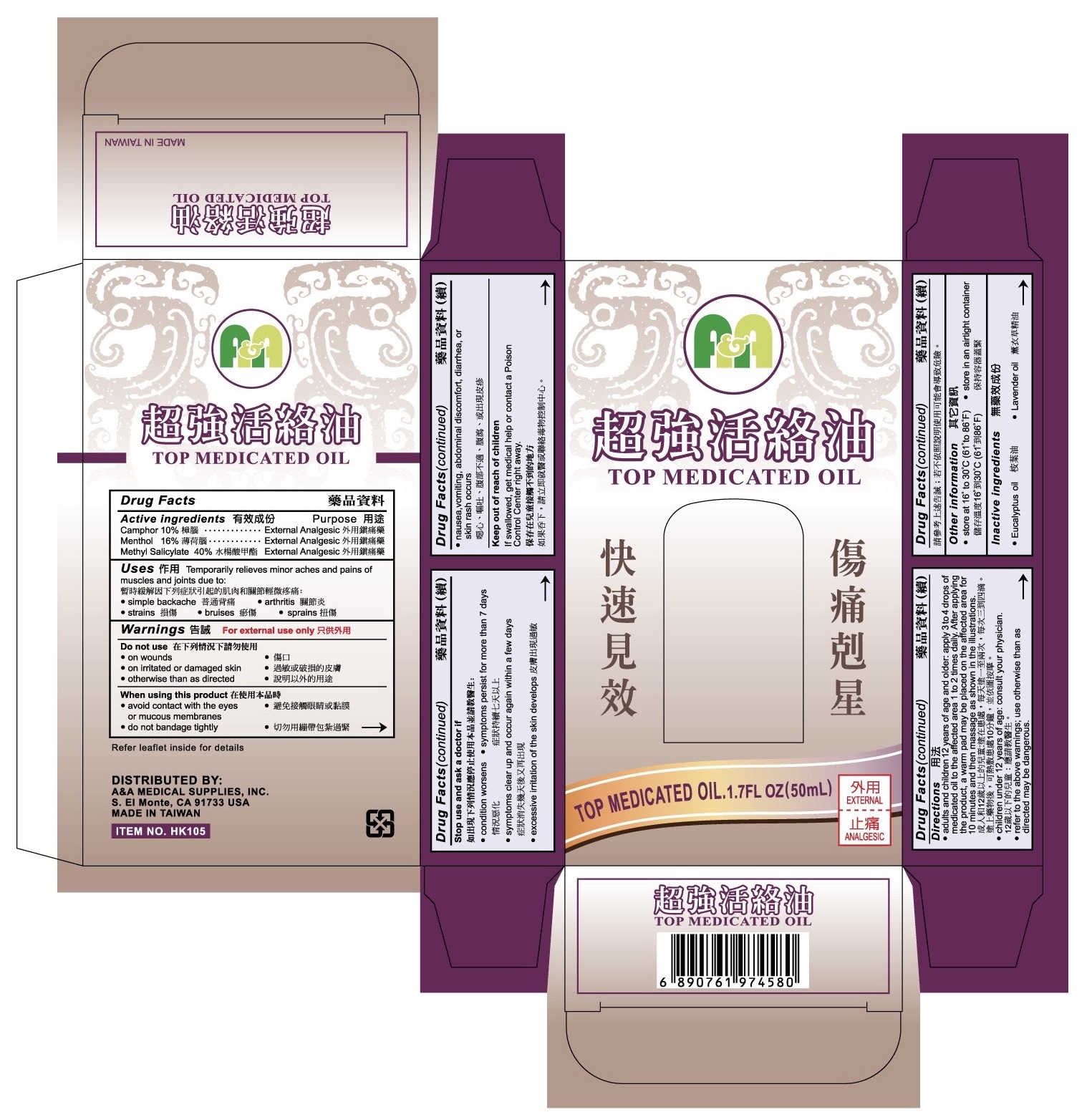 DRUG LABEL: Top Medicated Oil
NDC: 82198-0009 | Form: OIL
Manufacturer: Big 5 Nutrition LLC
Category: otc | Type: HUMAN OTC DRUG LABEL
Date: 20231121

ACTIVE INGREDIENTS: CAMPHOR (NATURAL) 10 mg/1 mL; MENTHOL, UNSPECIFIED FORM 16 mg/1 mL; METHYL SALICYLATE 40 mg/1 mL
INACTIVE INGREDIENTS: EUCALYPTUS OIL; LAVENDER OIL

TOP MEDICATED OIL

Active ingredients

Camphor 10%

Menthol 16%

Methyl Salicylate 40%

Purpose

External Analgesic

Uses

Temporarily relieves minor aches and pains of muscles and joints due to:

• simple backache • arthritis • strains • bruises • sprains

Warnings

For external use only

Do not use

• on wounds

• on irritated or damaged skin

• otherwise than as directed

When using this product

• avoid contact with the eyes or mucous membranes

• do not bandage tightly

Stop use and ask a doctor if

• condition worsens • symptoms persist for more than 7 days

• symptoms clear up and occur again within a few days

• excessive irritation of the skin develops

• nausea, vomiting, abdominal discomfort, diarrhea, or skin rashes occurs

Keep out of reach of children

If swallowed, get medical help or contact a Poison Control Center right away.

Directions

• adults and children 12 years of age and older: apply 3 to 4 drops of medicated oil to the affected area 1 to 2 times daily. After applying the product, a warm pad may be placed on the affected area for 10 minutes and then massage as shown in the illustrations.

• children under 12 years of age: consult your physician.

• refer to the above warnings; use otherwise than as directed may be dangerous.

Other information

• store at 16° to 30°C (61° to 86° F) • store in an airtight container

Inactive ingredients

• Eucalyptus oil • Lavender oil

DISTRIBUTED BY:

A&A MEDICAL SUPPLIES, INC.

S. El Monte, CA 91733 USA

MADE IN TAIWAN

ITEM NO. HK105